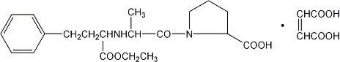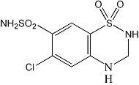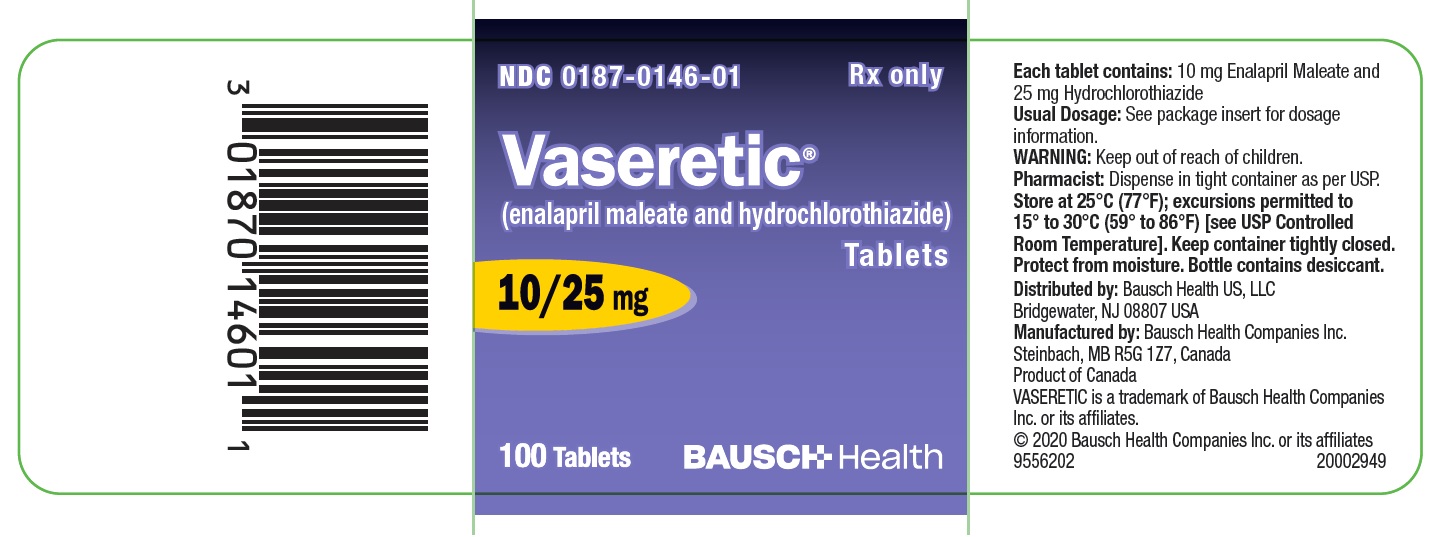 DRUG LABEL: Vaseretic
NDC: 0187-0146 | Form: TABLET
Manufacturer: Bausch Health US, LLC
Category: prescription | Type: HUMAN PRESCRIPTION DRUG LABEL
Date: 20200831

ACTIVE INGREDIENTS: Enalapril Maleate 10 mg/1 1; Hydrochlorothiazide 25 mg/1 1
INACTIVE INGREDIENTS: ferric oxide red; LACTOSE, UNSPECIFIED FORM; magnesium stearate; sodium bicarbonate; starch, corn

VASERETIC® Tablets
(enalapril maleate and hydrochlorothiazide)

WARNING: FETAL TOXICITY See full prescribing information for complete boxed warning.

- When pregnancy is detected, discontinue VASERETIC® as soon as possible.
- Drugs that act directly on the renin-angiotensin system can cause injury and death to the developing fetus. See WARNINGS: Fetal Toxicity

DESCRIPTION

VASERETIC® (enalapril maleate and hydrochlorothiazide) combines an angiotensin converting enzyme inhibitor, enalapril maleate, and a diuretic, hydrochlorothiazide.

Enalapril maleate is the maleate salt of enalapril, the ethyl ester of a long-acting angiotensin converting enzyme inhibitor, enalaprilat. Enalapril maleate is chemically described as (S)-1-[N-[1-(ethoxycarbonyl)-3-phenylpropyl]-L-alanyl]-L-proline, (Z)-2-butenedioate salt (1:1). Its empirical formula is C20H28N2O5•C4H4O4, and its structural formula is:

Enalapril maleate is a white to off-white crystalline powder with a molecular weight of 492.53. It is sparingly soluble in water, soluble in ethanol, and freely soluble in methanol.

Enalapril is a pro-drug; following oral administration, it is bioactivated by hydrolysis of the ethyl ester to enalaprilat, which is the active angiotensin converting enzyme inhibitor.

Hydrochlorothiazide is 6-chloro-3,4-dihydro-2H-1,2,4-benzothiadiazine-7-sulfonamide 1,1-dioxide. Its empirical formula is C7H8ClN3O4S2 and its structural formula is:

It is a white, or practically white, crystalline powder with a molecular weight of 297.74, which is slightly soluble in water, but freely soluble in sodium hydroxide solution.

VASERETIC is available in the tablet combination of enalapril maleate with hydrochlorothiazide: VASERETIC 10-25 mg, containing 10 mg enalapril maleate and 25 mg hydrochlorothiazide. Inactive ingredients are: iron oxide, lactose, magnesium stearate, sodium bicarbonate, and starch.

CLINICAL PHARMACOLOGY

As a result of its diuretic effects, hydrochlorothiazide increases plasma renin activity, increases aldosterone secretion, and decreases serum potassium. Administration of enalapril maleate blocks the renin-angiotensin-aldosterone axis and tends to reverse the potassium loss associated with the diuretic.

In clinical studies, the extent of blood pressure reduction seen with the combination of enalapril maleate and hydrochlorothiazide was approximately additive. The antihypertensive effect of VASERETIC was usually sustained for at least 24 hours.

Concomitant administration of enalapril maleate and hydrochlorothiazide has little, or no effect on the bioavailability of either drug. The combination tablet is bioequivalent to concomitant administration of the separate entities.

Enalapril Maleate

Mechanism of Action
Enalapril, after hydrolysis to enalaprilat, inhibits angiotensin-converting enzyme (ACE) in human subjects and animals. ACE is a peptidyl dipeptidase that catalyzes the conversion of angiotensin I to the vasoconstrictor substance, angiotensin II. Angiotensin II also stimulates aldosterone secretion by the adrenal cortex. Inhibition of ACE results in decreased plasma angiotensin II, which leads to decreased vasopressor activity and to decreased aldosterone secretion. Although the latter decrease is small, it results in small increases of serum potassium. In hypertensive patients treated with enalapril maleate alone for up to 48 weeks, mean increases in serum potassium of approximately 0.2 mEq/L were observed. In patients treated with enalapril maleate plus a thiazide diuretic, there was essentially no change in serum potassium (see PRECAUTIONS). Removal of angiotensin II negative feedback on renin secretion leads to increased plasma renin activity.

ACE is identical to kininase, an enzyme that degrades bradykinin. Whether increased levels of bradykinin, a potent vasodepressor peptide, play a role in the therapeutic effects of enalapril remains to be elucidated.

While the mechanism through which enalapril lowers blood pressure is believed to be primarily suppression of the renin-angiotensin-aldosterone system, enalapril is antihypertensive even in patients with low-renin hypertension. Although enalapril was antihypertensive in all races studied, black hypertensive patients (usually a low-renin hypertensive population) had a smaller average response to enalapril maleate monotherapy than non-black patients. In contrast, hydrochlorothiazide was more effective in black patients than enalapril. Concomitant administration of enalapril maleate and hydrochlorothiazide was equally effective in black and non-black patients.

Pharmacokinetics and Metabolism
Following oral administration of enalapril maleate, peak serum concentrations of enalapril occur within about one hour. Based on urinary recovery, the extent of absorption of enalapril is approximately 60 percent. Enalapril absorption is not influenced by the presence of food in the gastrointestinal tract. Following absorption, enalapril is hydrolyzed to enalaprilat, which is a more potent angiotensin converting enzyme inhibitor than enalapril; enalaprilat is poorly absorbed when administered orally. Peak serum concentrations of enalaprilat occur three to four hours after an oral dose of enalapril maleate. Excretion of enalaprilat and enalapril is primarily renal. Approximately 94 percent of the dose is recovered in the urine and feces as enalaprilat or enalapril. The principal components in urine are enalaprilat, accounting for about 40 percent of the dose, and intact enalapril. There is no evidence of metabolites of enalapril, other than enalaprilat.

The serum concentration profile of enalaprilat exhibits a prolonged terminal phase, apparently representing a small fraction of the administered dose that has been bound to ACE. The amount bound does not increase with dose, indicating a saturable site of binding. The effective half-life for accumulation of enalaprilat following multiple doses of enalapril maleate is 11 hours.

The disposition of enalapril and enalaprilat in patients with renal insufficiency is similar to that in patients with normal renal function until the glomerular filtration rate is 30 mL/min or less. With glomerular filtration rate ≤30 mL/min, peak and trough enalaprilat levels increase, time to peak concentration increases and time to steady state may be delayed. The effective half-life of enalaprilat following multiple doses of enalapril maleate is prolonged at this level of renal insufficiency. Enalaprilat is dialyzable at the rate of 62 mL/min.

Studies in dogs indicate that enalapril crosses the blood-brain barrier poorly, if at all; enalaprilat does not enter the brain. Multiple doses of enalapril maleate in rats do not result in accumulation in any tissues. Milk of lactating rats contains radioactivity following administration of ^14C enalapril maleate. Radioactivity was found to cross the placenta following administration of labeled drug to pregnant hamsters.

Pharmacodynamics
Administration of enalapril maleate to patients with hypertension of severity ranging from mild to severe results in a reduction of both supine and standing blood pressure usually with no orthostatic component. Symptomatic postural hypotension is infrequent with enalapril alone but it can be anticipated in volume-depleted patients, such as patients treated with diuretics. In clinical trials with enalapril and hydrochlorothiazide administered concurrently, syncope occurred in 1.3 percent of patients (see WARNINGS and DOSAGE AND ADMINISTRATION).

In most patients studied, after oral administration of a single dose of enalapril maleate, onset of antihypertensive activity was seen at one hour with peak reduction of blood pressure achieved by four to six hours.

At recommended doses, antihypertensive effects of enalapril maleate monotherapy have been maintained for at least 24 hours. In some patients the effects may diminish toward the end of the dosing interval; this was less frequently observed with concomitant administration of enalapril maleate and hydrochlorothiazide.

Achievement of optimal blood pressure reduction may require several weeks of enalapril therapy in some patients.

The antihypertensive effects of enalapril have continued during long-term therapy. Abrupt withdrawal of enalapril has not been associated with a rapid increase in blood pressure.

In hemodynamic studies in patients with essential hypertension, blood pressure reduction produced by enalapril was accompanied by a reduction in peripheral arterial resistance with an increase in cardiac output and little or no change in heart rate. Following administration of enalapril maleate, there is an increase in renal blood flow; glomerular filtration rate is usually unchanged. The effects appear to be similar in patients with renovascular hypertension.

In a clinical pharmacology study, indomethacin or sulindac was administered to hypertensive patients receiving enalapril maleate. In this study there was no evidence of a blunting of the antihypertensive action of enalapril maleate (see PRECAUTIONS, Drug Interactions, Enalapril Maleate).

Hydrochlorothiazide

The mechanism of the antihypertensive effect of thiazides is unknown. Thiazides do not usually affect normal blood pressure. Hydrochlorothiazide is a diuretic and antihypertensive. It affects the distal renal tubular mechanism of electrolyte reabsorption. Hydrochlorothiazide increases excretion of sodium and chloride in approximately equivalent amounts. Natriuresis may be accompanied by some loss of potassium and bicarbonate. After oral use diuresis begins within two hours, peaks in about four hours and lasts about 6 to 12 hours. Hydrochlorothiazide is not metabolized but is eliminated rapidly by the kidney. When plasma levels have been followed for at least 24 hours, the plasma half-life has been observed to vary between 5.6 and 14.8 hours. At least 61 percent of the oral dose is eliminated unchanged within 24 hours. Hydrochlorothiazide crosses the placental but not the blood-brain barrier.

INDICATIONS AND USAGE

VASERETIC is indicated for the treatment of hypertension.

This fixed dose combination is not indicated for initial treatment (see DOSAGE AND ADMINISTRATION).

In using VASERETIC, consideration should be given to the fact that another angiotensin converting enzyme inhibitor, captopril, has caused agranulocytosis, particularly in patients with renal impairment or collagen vascular disease, and that available data are insufficient to show that enalapril does not have a similar risk (see WARNINGS).

In considering use of VASERETIC, it should be noted that black patients receiving ACE inhibitors have been reported to have a higher incidence of angioedema compared to non-blacks (see WARNINGS, Head and Neck Angioedema).

CONTRAINDICATIONS

VASERETIC is contraindicated in patients who are hypersensitive to any component of this product and in patients with a history of angioedema related to previous treatment with an angiotensin converting enzyme inhibitor and in patients with hereditary or idiopathic angioedema. Because of the hydrochlorothiazide component, this product is contraindicated in patients with anuria or hypersensitivity to other sulfonamide-derived drugs.

VASERETIC is contraindicated in combination with a neprilysin inhibitor (e.g., sacubitril). Do not administer VASERETIC within 36 hours of switching to or from sacubitril/valsartan, a neprilysin inhibitor (see WARNINGS).

Do not co-administer aliskiren with VASERETIC in patients with diabetes (see PRECAUTIONS, Drug Interactions).

WARNINGS

General

Enalapril Maleate

Hypotension: Excessive hypotension was rarely seen in uncomplicated hypertensive patients but is a possible consequence of enalapril use in severely salt/volume depleted persons such as those treated vigorously with diuretics or patients on dialysis.

Syncope has been reported in 1.3 percent of patients receiving VASERETIC. In patients receiving enalapril alone, the incidence of syncope is 0.5 percent. The overall incidence of syncope may be reduced by proper titration of the individual components (see PRECAUTIONS, Drug Interactions, ADVERSE REACTIONS and DOSAGE AND ADMINISTRATION).

In patients with severe congestive heart failure, with or without associated renal insufficiency, excessive hypotension has been observed and may be associated with oliguria and/or progressive azotemia, and rarely with acute renal failure and/or death. Because of the potential fall in blood pressure in these patients, therapy should be started under very close medical supervision. Such patients should be followed closely for the first two weeks of treatment and whenever the dose of enalapril and/or diuretic is increased. Similar considerations may apply to patients with ischemic heart or cerebrovascular disease, in whom an excessive fall in blood pressure could result in a myocardial infarction or cerebrovascular accident.

If hypotension occurs, the patient should be placed in the supine position and, if necessary, receive an intravenous infusion of normal saline. A transient hypotensive response is not a contraindication to further doses, which usually can be given without difficulty once the blood pressure has increased after volume expansion.

Anaphylactoid and Possibly Related Reactions

Presumably because angiotensin-converting enzyme inhibitors affect the metabolism of eicosanoids and polypeptides, including endogenous bradykinin, patients receiving ACE inhibitors (including VASERETIC) may be subject to a variety of adverse reactions, some of them serious.

Head and Neck Angioedema
Angioedema of the face, extremities, lips, tongue, glottis and/or larynx has been reported in patients treated with angiotensin converting enzyme inhibitors, including enalapril. This may occur at any time during treatment. In such cases VASERETIC should be promptly discontinued and appropriate therapy and monitoring should be provided until complete and sustained resolution of signs and symptoms has occurred. In instances where swelling has been confined to the face and lips the condition has generally resolved without treatment, although antihistamines have been useful in relieving symptoms. Angioedema associated with laryngeal edema may be fatal. Where there is involvement of the tongue, glottis or larynx, likely to cause airway obstruction, appropriate therapy, e.g., subcutaneous epinephrine solution 1:1000 (0.3 mL to 0.5 mL) and/or measures necessary to ensure a patent airway, should be promptly provided (see ADVERSE REACTIONS).

Patients receiving coadministration of ACE inhibitor and mTOR (mammalian target of rapamycin) inhibitor (e.g., temsirolimus, sirolimus, everolimus) therapy or a neprilysin inhibitor may be at increased risk for angioedema (see PRECAUTIONS).

Intestinal Angioedema
Intestinal angioedema has been reported in patients treated with ACE inhibitors. These patients presented with abdominal pain (with or without nausea or vomiting); in some cases there was no prior history of facial angioedema and C-1 esterase levels were normal. The angioedema was diagnosed by procedures including abdominal CT scan or ultrasound, or at surgery, and symptoms resolved after stopping the ACE inhibitor. Intestinal angioedema should be included in the differential diagnosis of patients on ACE inhibitors presenting with abdominal pain.

Patients with a history of angioedema unrelated to ACE inhibitor therapy may be at increased risk of angioedema while receiving an ACE inhibitor (see also INDICATIONS AND USAGE and CONTRAINDICATIONS).

Anaphylactoid Reactions During Desensitization
Two patients undergoing desensitizing treatment with hymenoptera venom while receiving ACE inhibitors sustained life-threatening anaphylactoid reactions. In the same patients, these reactions were avoided when ACE inhibitors were temporarily withheld, but they reappeared upon inadvertent rechallenge.

Anaphylactoid Reactions During Membrane Exposure
Anaphylactoid reactions have been reported in patients dialyzed with high-flux membranes and treated concomitantly with an ACE inhibitor. Anaphylactoid reactions have also been reported in patients undergoing low-density lipoprotein apheresis with dextran sulfate absorption.

Neutropenia/Agranulocytosis
Another angiotensin converting enzyme inhibitor, captopril, has been shown to cause agranulocytosis and bone marrow depression, rarely in uncomplicated patients but more frequently in patients with renal impairment especially if they also have a collagen vascular disease. Available data from clinical trials of enalapril are insufficient to show that enalapril does not cause agranulocytosis at similar rates. Marketing experience has revealed cases of neutropenia or agranulocytosis in which a causal relationship to enalapril cannot be excluded. Periodic monitoring of white blood cell counts in patients with collagen vascular disease and renal disease should be considered.

Hepatic Failure
Rarely, ACE inhibitors have been associated with a syndrome that starts with cholestatic jaundice and progresses to fulminant hepatic necrosis, and (sometimes) death. The mechanism of this syndrome is not understood. Patients receiving ACE inhibitors who develop jaundice or marked elevations of hepatic enzymes should discontinue the ACE inhibitor and receive appropriate medical follow-up.

Hydrochlorothiazide

Thiazides should be used with caution in severe renal disease. In patients with renal disease, thiazides may precipitate azotemia. Cumulative effects of the drug may develop in patients with impaired renal function.

Thiazides should be used with caution in patients with impaired hepatic function or progressive liver disease, since minor alterations of fluid and electrolyte balance may precipitate hepatic coma.

Sensitivity reactions may occur in patients with or without a history of allergy or bronchial asthma.

The possibility of exacerbation or activation of systemic lupus erythematosus has been reported.

Lithium generally should not be given with thiazides (see PRECAUTIONS, Drug Interactions, Enalapril Maleate and Hydrochlorothiazide).

Acute Myopia and Secondary Angle-Closure Glaucoma

Hydrochlorothiazide, a sulfonamide, can cause an idiosyncratic reaction, resulting in acute transient myopia and acute angle-closure glaucoma. Symptoms include acute onset of decreased visual acuity or ocular pain and typically occur within hours to weeks of drug initiation. Untreated acute angle-closure glaucoma can lead to permanent vision loss. The primary treatment is to discontinue hydrochlorothiazide as rapidly as possible. Prompt medical or surgical treatments may need to be considered if the intraocular pressure remains uncontrolled. Risk factors for developing acute angle-closure glaucoma may include a history of sulfonamide or penicillin allergy.

Fetal Toxicity

Enalapril Maleate

Use of drugs that act on the renin-angiotensin system during the second and third trimesters of pregnancy reduces fetal renal function and increases fetal and neonatal morbidity and death. Resulting oligohydramnios can be associated with fetal lung hypoplasia and skeletal deformations. Potential neonatal adverse effects include skull hypoplasia, anuria, hypotension, renal failure, and death. When pregnancy is detected, discontinue VASERETIC as soon as possible. These adverse outcomes are usually associated with use of these drugs in the second and third trimester of pregnancy. Most epidemiologic studies examining fetal abnormalities after exposure to antihypertensive use in the first trimester have not distinguished drugs affecting the renin-angiotensin system from other antihypertensive agents. Appropriate management of maternal hypertension during pregnancy is important to optimize outcomes for both mother and fetus.

In the unusual case that there is no appropriate alternative to therapy with drugs affecting the renin-angiotensin system for a particular patient, apprise the mother of the potential risk to the fetus. Perform serial ultrasound examinations to assess the intra-amniotic environment. If oligohydramnios is observed, discontinue VASERETIC, unless it is considered lifesaving for the mother. Fetal testing may be appropriate, based on the week of pregnancy. Patients and physicians should be aware, however that oligohydramnios may not appear until after the fetus has sustained irreversible injury. Closely observe infants with histories of in utero exposure to VASERETIC for hypotension, oliguria, and hyperkalemia (see PRECAUTIONS, Pediatric Use).

No teratogenic effects of enalapril were seen in studies of pregnant rats and rabbits. On a body surface area basis, the doses used were 57 times and 12 times, respectively, the MRHDD.

Enalapril-Hydrochlorothiazide

There was no teratogenicity in mice given up to 30 mg/kg/day or in rats given up to 90 mg/kg/day of enalapril in combination with 10 mg/kg/day of hydrochlorothiazide. These doses of enalapril are 4.3 and 26 times (mice and rats, respectively) the maximum recommended human daily dose (MRHDD) when compared on a body surface area basis (mg/m^2); the dose of hydrochlorothiazide is 0.8 times (in mice) and 1.6 times (in rats) the MRHDD. At these doses, fetotoxicity expressed as a decrease in average fetal weight occurred in both species. No fetotoxicity occurred at lower doses; 30/10 mg/kg/day of enalapril-hydrochlorothiazide in rats and 10/10 mg/kg/day of enalapril-hydrochlorothiazide in mice.

When used in pregnancy during the second and third trimesters, ACE inhibitors can cause injury and even death to the developing fetus. When pregnancy is detected, VASERETIC should be discontinued as soon as possible (see Fetal Toxicity, Enalapril Maleate).

Hydrochlorothiazide

Studies in which hydrochlorothiazide was orally administered to pregnant mice and rats during their respective periods of major organogenesis at doses up to 3000 and 1000 mg/kg/day, respectively, provided no evidence of harm to the fetus. These doses are more than 150 times the MRHDD on a body surface area basis. Thiazides cross the placental barrier and appear in cord blood. There is a risk of fetal or neonatal jaundice, thrombocytopenia and possibly other adverse reactions that have occurred in adults.

PRECAUTIONS

General

Enalapril Maleate

Aortic Stenosis/Hypertrophic Cardiomyopathy: As with all vasodilators, enalapril should be given with caution to patients with obstruction in the outflow tract of the left ventricle.

Impaired Renal Function
As a consequence of inhibiting the renin-angiotensin-aldosterone system, changes in renal function may be anticipated in susceptible individuals. In patients with severe congestive heart failure whose renal function may depend on the activity of the renin-angiotensin-aldosterone system, treatment with angiotensin converting enzyme inhibitors, including enalapril, may be associated with oliguria and/or progressive azotemia and rarely with acute renal failure and/or death (see PRECAUTIONS, Drug Interactions).

In clinical studies in hypertensive patients with unilateral or bilateral renal artery stenosis, increases in blood urea nitrogen and serum creatinine were observed in 20 percent of patients. These increases were almost always reversible upon discontinuation of enalapril and/or diuretic therapy. In such patients renal function should be monitored during the first few weeks of therapy.

Some patients with hypertension or heart failure with no apparent pre-existing renal vascular disease have developed increases in blood urea and serum creatinine, usually minor and transient, especially when enalapril has been given concomitantly with a diuretic. This is more likely to occur in patients with pre-existing renal impairment. Dosage reduction of enalapril and/or discontinuation of the diuretic may be required.

Evaluation of the hypertensive patient should always include assessment of renal function.

Hyperkalemia
Elevated serum potassium (greater than 5.7 mEq/L) was observed in approximately one percent of hypertensive patients in clinical trials treated with enalapril alone. In most cases these were isolated values which resolved despite continued therapy, although hyperkalemia was a cause of discontinuation of therapy in 0.28 percent of hypertensive patients. Hyperkalemia was less frequent (approximately 0.1 percent) in patients treated with enalapril plus hydrochlorothiazide. Risk factors for the development of hyperkalemia include renal insufficiency, diabetes mellitus, and the concomitant use of potassium-sparing diuretics, potassium supplements and/or potassium-containing salt substitutes, which should be used cautiously, if at all, with enalapril (see Drug Interactions).

Cough
Presumably due to the inhibition of the degradation of endogenous bradykinin, persistent nonproductive cough has been reported with all ACE inhibitors, always resolving after discontinuation of therapy. ACE inhibitor-induced cough should be considered in the differential diagnosis of cough.

Surgery/Anesthesia
In patients undergoing major surgery or during anesthesia with agents that produce hypotension, enalapril may block angiotensin II formation secondary to compensatory renin release. If hypotension occurs and is considered to be due to this mechanism, it can be corrected by volume expansion.

Hydrochlorothiazide

Periodic determination of serum electrolytes to detect possible electrolyte imbalance should be performed at appropriate intervals. All patients receiving thiazide therapy should be observed for clinical signs of fluid or electrolyte imbalance: hyponatremia, hypochloremic alkalosis, and hypokalemia. Serum and urine electrolyte determinations are particularly important when the patient is vomiting excessively or receiving parenteral fluids. Warning signs or symptoms of fluid and electrolyte imbalance, irrespective of cause, include dryness of mouth, thirst, weakness, lethargy, drowsiness, restlessness, confusion, seizures, muscle pains or cramps, muscular fatigue, hypotension, oliguria, tachycardia, and gastrointestinal disturbances such as nausea and vomiting.

Hypokalemia may develop, especially with brisk diuresis, when severe cirrhosis is present, or after prolonged therapy. Interference with adequate oral electrolyte intake will also contribute to hypokalemia. Hypokalemia may cause cardiac arrhythmia and may also sensitize or exaggerate the response of the heart to the toxic effects of digitalis (e.g., increased ventricular irritability). Because enalapril reduces the production of aldosterone, concomitant therapy with enalapril attenuates the diuretic-induced potassium loss (see Drug Interactions, Agents Increasing Serum Potassium).

Although any chloride deficit is generally mild and usually does not require specific treatment except under extraordinary circumstances (as in liver disease or renal disease), chloride replacement may be required in the treatment of metabolic alkalosis.

Dilutional hyponatremia may occur in edematous patients in hot weather; appropriate therapy is water restriction, rather than administration of salt except in rare instances when the hyponatremia is life-threatening. In actual salt depletion, appropriate replacement is the therapy of choice.

Hyperuricemia may occur or frank gout may be precipitated in certain patients receiving thiazide therapy.

In diabetic patients dosage adjustments of insulin or oral hypoglycemic agents may be required. Hyperglycemia may occur with thiazide diuretics. Thus latent diabetes mellitus may become manifest during thiazide therapy.

The antihypertensive effects of the drug may be enhanced in the post-sympathectomy patient.

If progressive renal impairment becomes evident consider withholding or discontinuing diuretic therapy.

Thiazides have been shown to increase the urinary excretion of magnesium; this may result in hypomagnesemia.

Thiazides may decrease urinary calcium excretion. Thiazides may cause intermittent and slight elevation of serum calcium in the absence of known disorders of calcium metabolism. Marked hypercalcemia may be evidence of hidden hyperparathyroidism. Thiazides should be discontinued before carrying out tests for parathyroid function.

Increases in cholesterol and triglyceride levels may be associated with thiazide diuretic therapy.

Information for Patients

Angioedema
Angioedema, including laryngeal edema, may occur at any time during treatment with angiotensin converting enzyme inhibitors, including enalapril. Patients should be so advised and told to report immediately any signs or symptoms suggesting angioedema (swelling of face, extremities, eyes, lips, tongue, difficulty in swallowing or breathing) and to take no more drug until they have consulted with the prescribing physician.

Hypotension
Patients should be cautioned to report lightheadedness especially during the first few days of therapy. If actual syncope occurs, the patients should be told to discontinue the drug until they have consulted with the prescribing physician.

All patients should be cautioned that excessive perspiration and dehydration may lead to an excessive fall in blood pressure because of reduction in fluid volume. Other causes of volume depletion such as vomiting or diarrhea may also lead to a fall in blood pressure; patients should be advised to consult with the physician.

Hyperkalemia
Patients should be told not to use salt substitutes containing potassium without consulting their physician.

Neutropenia
Patients should be told to report promptly any indication of infection (e.g., sore throat, fever) which may be a sign of neutropenia.

Pregnancy
Female patients of childbearing age should be told about the consequences of exposure to VASERETIC during pregnancy. Discuss treatment options with women planning to become pregnant. Patients should be asked to report pregnancies to their physicians as soon as possible.

NOTE: As with many other drugs, certain advice to patients being treated with VASERETIC is warranted. This information is intended to aid in the safe and effective use of this medication. It is not a disclosure of all possible adverse or intended effects.

Non-melanoma Skin Cancer
Instruct patients taking hydrochlorothiazide to protect skin from the sun and undergo regular skin cancer screening.

Drug Interactions
Neprilysin Inhibitors

Patients taking concomitant neprilysin inhibitors may be at increased risk for angioedema. (see WARNINGS).

Enalapril Maleate

Dual Blockade of the Renin-Angiotensin System (RAS)

Dual blockade of the RAS with angiotensin receptor blockers, ACE inhibitors, or aliskiren is associated with increased risks of hypotension, hyperkalemia, and changes in renal function (including acute renal failure) compared to monotherapy. Most patients receiving the combination of two RAS inhibitors do not obtain any additional benefit compared to monotherapy. In general, avoid combined use of RAS inhibitors. Closely monitor blood pressure, renal function, and electrolytes in patients on VASERETIC and other agents that affect the RAS.

Do not coadminister aliskiren with VASERETIC in patients with diabetes. Avoid use of aliskiren with VASERETIC in patients with renal impairment (GFR <60 mL/min).

Hypotension – Patients on Diuretic Therapy
Patients on diuretics and especially those in whom diuretic therapy was recently instituted, may occasionally experience an excessive reduction of blood pressure after initiation of therapy with enalapril. The possibility of hypotensive effects with enalapril can be minimized by either discontinuing the diuretic or increasing the salt intake prior to initiation of treatment with enalapril. If it is necessary to continue the diuretic, provide medical supervision for at least two hours and until blood pressure has stabilized for at least an additional hour (see WARNINGS and DOSAGE AND ADMINISTRATION).

Agents Causing Renin Release
The antihypertensive effect of enalapril is augmented by antihypertensive agents that cause renin release (e.g., diuretics).

Non-steroidal Anti-inflammatory Agents Including Selective Cyclooxygenase-2 Inhibitors (COX-2 Inhibitors)
In patients who are elderly, volume-depleted (including those on diuretic therapy), or with compromised renal function, coadministration of NSAIDs, including selective COX-2 inhibitors, with ACE inhibitors, including enalapril, may result in deterioration of renal function, including possible acute renal failure. These effects are usually reversible. Monitor renal function periodically in patients receiving enalapril and NSAID therapy.

In a clinical pharmacology study, indomethacin or sulindac was administered to hypertensive patients receiving enalapril maleate. In this study there was no evidence of a blunting of the antihypertensive action of enalapril maleate. However, reports suggest that NSAIDs may diminish the antihypertensive effect of ACE inhibitors.

Other Cardiovascular Agents
Enalapril has been used concomitantly with beta adrenergic-blocking agents, methyldopa, nitrates, calcium-blocking agents, hydralazine and prazosin without evidence of clinically significant adverse interactions.

Agents Increasing Serum Potassium
Enalapril attenuates diuretic-induced potassium loss. Potassium-sparing diuretics (e.g., spironolactone, triamterene, or amiloride), potassium supplements, or potassium-containing salt substitutes may lead to significant increases in serum potassium. Therefore, if concomitant use of these agents is indicated because of demonstrated hypokalemia they should be used with caution and with frequent monitoring of serum potassium.

Lithium
Lithium toxicity has been reported in patients receiving lithium concomitantly with drugs which cause elimination of sodium, including ACE inhibitors. A few cases of lithium toxicity have been reported in patients receiving concomitant enalapril and lithium and were reversible upon discontinuation of both drugs. It is recommended that serum lithium levels be monitored frequently if enalapril is administered concomitantly with lithium.

Gold
Nitritoid reactions (symptoms include facial flushing, nausea, vomiting and hypotension) have been reported rarely in patients on therapy with injectable gold (sodium aurothiomalate) and concomitant ACE inhibitor therapy including VASERETIC.

mTOR (mammalian target of rapamycin) inhibitors: Patients receiving coadministration of ACE inhibitor and mTOR inhibitor (e.g., temsirolimus, sirolimus, everolimus) therapy may be at increased risk for angioedema (see WARNINGS).

Hydrochlorothiazide

When administered concurrently the following drugs may interact with thiazide diuretics:

Alcohol, barbiturates, or narcotics
Potentiation of orthostatic hypotension may occur.

Anti-diabetic drugs (oral agents and insulin)
Dosage adjustment of the anti-diabetic drug may be required.

Other anti-hypertensive drugs
Additive effect or potentiation.

Cholestyramine and colestipol resins
Absorption of hydrochlorothiazide is impaired in the presence of anionic exchange resins. Single doses of either cholestyramine or colestipol resins bind the hydrochlorothiazide and reduce its absorption from the gastrointestinal tract by up to 85 and 43 percent, respectively.

Corticosteroids, ACTH
Intensified electrolyte depletion, particularly hypokalemia.

Pressor amines (e.g., norepinephrine)
Possible decreased response to pressor amines but not sufficient to preclude their use.

Skeletal muscle relaxants, nondepolarizing (e.g., tubocurarine)
Possible increased responsiveness to the muscle relaxant.

Lithium
Should not generally be given with diuretics. Diuretic agents reduce the renal clearance of lithium and add a high risk of lithium toxicity. Refer to the package insert for lithium preparations before use of such preparations with VASERETIC.

Non-steroidal Anti-inflammatory Drugs
In some patients, the administration of a non-steroidal anti-inflammatory agent can reduce the diuretic, natriuretic, and antihypertensive effects of loop, potassium-sparing and thiazide diuretics. Therefore, when VASERETIC and non-steroidal anti-inflammatory agents are used concomitantly, the patient should be observed closely to determine if the desired effect of the diuretic is obtained.

Carcinogenesis, Mutagenesis, Impairment of Fertility

Enalapril in combination with hydrochlorothiazide was not mutagenic in the Ames microbial mutagen test with or without metabolic activation. Enalapril-hydrochlorothiazide did not produce DNA single strand breaks in an in vitro alkaline elution assay in rat hepatocytes or chromosomal aberrations in an in vivo mouse bone marrow assay.

Enalapril Maleate

There was no evidence of a tumorigenic effect when enalapril was administered for 106 weeks to male and female rats at doses up to 90 mg/kg/day or for 94 weeks to male and female mice at doses up to 90 and 180 mg/kg/day, respectively. These doses are 26 times (in rats and female mice) and 13 times (in male mice) the maximum recommended human daily dose (MRHDD) when compared on a body surface area basis.

Neither enalapril maleate nor the active diacid was mutagenic in the Ames microbial mutagen test with or without metabolic activation. Enalapril was also negative in the following genotoxicity studies: rec-assay, reverse mutation assay with E. coli, sister chromatid exchange with cultured mammalian cells, and the micronucleus test with mice, as well as in an in vivo cytogenic study using mouse bone marrow.

There were no adverse effects on reproductive performance of male and female rats treated with up to 90 mg/kg/day of enalapril (26 times the MRHDD when compared on a body surface area basis).

Hydrochlorothiazide

Two year feeding studies in mice and rats conducted under the auspices of the National Toxicology Program (NTP) uncovered no evidence of a carcinogenic potential of hydrochlorothiazide in female mice at doses up to approximately 600 mg/kg/day (53 times the MRHDD when compared on a body surface area basis) or in male and female rats at doses up to approximately 100 mg/kg/day (18 times the MRHDD when compared on a body surface area basis). The NTP, however, found equivocal evidence for hepatocarcinogenicity in male mice.

Hydrochlorothiazide was not genotoxic in vitro in the Ames mutagenicity assay of Salmonella typhimurium strains TA 98, TA 100, TA 1535, TA 1537, and TA 1538 and in the Chinese Hamster Ovary (CHO) test for chromosomal aberrations, or in vivo in assays using mouse germinal cell chromosomes, Chinese hamster bone marrow chromosomes, and the Drosophila sex-linked recessive lethal trait gene. Positive test results were obtained only in the in vitro CHO Sister Chromatid Exchange (clastogenicity) and in the Mouse Lymphoma Cell (mutagenicity) assays, using concentrations of hydrochlorothiazide from 43 to 1300 mcg/mL, and in the Aspergillus nidulans non-disjunction assay at an unspecified concentration.

Hydrochlorothiazide had no adverse effects on the fertility of mice and rats of either sex in studies wherein these species were exposed, via their diet, to doses of up to 100 and 4 mg/kg, respectively, prior to mating and throughout gestation. In mice and rats these doses are 9 times and 0.7 times, respectively, the MRHDD when compared on a body surface area basis.

Pregnancy

Nursing Mothers

Enalapril, enalaprilat, and hydrochlorothiazide have been detected in human breast milk. Because of the potential for serious reactions in nursing infants from either drug, a decision should be made whether to discontinue nursing or to discontinue VASERETIC, taking into account the importance of the drug to the mother.

Pediatric Use

Neonates with a history of in utero exposure to VASERETIC:

If oliguria or hypotension occurs, direct attention toward support of blood pressure and renal perfusion. Exchange transfusions or dialysis may be required as a means of reversing hypotension and/or substituting for disordered renal function. Enalapril, which crosses the placenta, has been removed from neonatal circulation by peritoneal dialysis with some clinical benefit, and theoretically may be removed by exchange transfusion, although there is no experience with the latter procedure.

Safety and effectiveness in pediatric patients have not been established.

Geriatric Use

Clinical studies of VASERETIC did not include sufficient numbers of subjects aged 65 and over to determine whether they respond differently from younger subjects. Other reported clinical experience has not identified differences in responses between the elderly and younger patients. In general, dose selection for an elderly patient should be cautious, usually starting at the low end of the dosing range, reflecting the greater frequency of decreased hepatic, renal, or cardiac function, and of concomitant disease or other drug therapy.

This drug is known to be substantially excreted by the kidney, and the risk of toxic reactions to this drug may be greater in patients with impaired renal function. Because elderly patients are more likely to have decreased renal function, care should be taken in dose selection. Evaluation of the hypertensive patient should always include assessment of renal function (see DOSAGE AND ADMINISTRATION).

ADVERSE REACTIONS

VASERETIC has been evaluated for safety in more than 1500 patients, including over 300 patients treated for one year or more. In clinical trials with VASERETIC no adverse experiences peculiar to this combination drug have been observed. Adverse experiences that have occurred have been limited to those that have been previously reported with enalapril or hydrochlorothiazide.

The most frequent clinical adverse experiences in controlled trials were: dizziness (8.6 percent), headache (5.5 percent), fatigue (3.9 percent) and cough (3.5 percent). Generally, adverse experiences were mild and transient in nature. Adverse experiences occurring in greater than two percent of patients treated with VASERETIC in controlled clinical trials are shown below.

 | Percent of Patients in Controlled Studies
 | VASERETIC (n=1580) Incidence (discontinuation) | Placebo (n=230) Incidence
Dizziness | 8.6 (0.7) | 4.3
Headache | 5.5 (0.4) | 9.1
Fatigue | 3.9 (0.8) | 2.6
Cough | 3.5 (0.4) | 0.9
Muscle Cramps | 2.7 (0.2) | 0.9
Nausea | 2.5 (0.4) | 1.7
Asthenia | 2.4 (0.3) | 0.9
Orthostatic Effects | 2.3 (<0.1) | 0.0
Impotence | 2.2 (0.5) | 0.5
Diarrhea | 2.1 (<0.1) | 1.7

Clinical adverse experiences occurring in 0.5 to 2.0 percent of patients in controlled trials included:

Body as a Whole: Syncope, chest pain, abdominal pain
Cardiovascular: Orthostatic hypotension, palpitation, tachycardia
Digestive: Vomiting, dyspepsia, constipation, flatulence, dry mouth
Nervous/Psychiatric: Insomnia, nervousness, paresthesia, somnolence, vertigo
Skin: Pruritus, rash
Other: Dyspnea, gout, back pain, arthralgia, diaphoresis, decreased libido, tinnitus, urinary tract infection

Angioedema: Angioedema has been reported in patients receiving VASERETIC, with an incidence higher in black than in non-black patients. Angioedema associated with laryngeal edema may be fatal. If angioedema of the face, extremities, lips, tongue, glottis and/or larynx occurs, treatment with VASERETIC should be discontinued and appropriate therapy instituted immediately (see WARNINGS).

Hypotension: In clinical trials, adverse effects relating to hypotension occurred as follows: hypotension (0.9 percent), orthostatic hypotension (1.5 percent), other orthostatic effects (2.3 percent). In addition syncope occurred in 1.3 percent of patients (see WARNINGS).

Cough: See PRECAUTIONS, Cough.

Clinical Laboratory Test Findings

Serum Electrolytes: See PRECAUTIONS.

Creatinine, Blood Urea Nitrogen: In controlled clinical trials minor increases in blood urea nitrogen and serum creatinine, reversible upon discontinuation of therapy, were observed in about 0.6 percent of patients with essential hypertension treated with VASERETIC. More marked increases have been reported in other enalapril experience. Increases are more likely to occur in patients with renal artery stenosis (see PRECAUTIONS).

Serum Uric Acid, Glucose, Magnesium, and Calcium: See PRECAUTIONS.

Hemoglobin and Hematocrit: Small decreases in hemoglobin and hematocrit (mean decreases of approximately 0.3 g percent and 1.0 vol percent, respectively) occur frequently in hypertensive patients treated with VASERETIC but are rarely of clinical importance unless another cause of anemia coexists. In clinical trials, less than 0.1 percent of patients discontinued therapy due to anemia.

Liver Function Tests: Rarely, elevations of liver enzymes and/or serum bilirubin have occurred (see WARNINGS, Hepatic Failure).

Other adverse reactions that have been reported with the individual components are listed below and, within each category, are in order of decreasing severity.

Enalapril Maleate – Enalapril has been evaluated for safety in more than 10,000 patients. In clinical trials adverse reactions which occurred with enalapril were also seen with VASERETIC. However, since enalapril has been marketed, the following adverse reactions have been reported: Body As A Whole: Anaphylactoid reactions (see WARNINGS, Anaphylactoid Reactions During Membrane Exposure); Cardiovascular: Cardiac arrest; myocardial infarction or cerebrovascular accident, possibly secondary to excessive hypotension in high risk patients (see WARNINGS, Hypotension); pulmonary embolism and infarction; pulmonary edema; rhythm disturbances including atrial tachycardia and bradycardia; atrial fibrillation; hypotension; angina pectoris, Raynaud's phenomenon; Digestive: Ileus, pancreatitis, hepatic failure, hepatitis (hepatocellular [proven on rechallenge] or cholestatic jaundice) (see WARNINGS, Hepatic Failure), melena, anorexia, glossitis, stomatitis, dry mouth; Hematologic: Rare cases of neutropenia, thrombocytopenia and bone marrow depression. Hemolytic anemia, including cases of hemolysis in patients with G6PD deficiency, has been reported; a causal relationship to enalapril cannot be excluded. Nervous System/Psychiatric: Depression, confusion, ataxia, peripheral neuropathy (e.g., paresthesia, dysesthesia), dream abnormality; Urogenital: Renal failure, oliguria, renal dysfunction, (see PRECAUTIONS and DOSAGE AND ADMINISTRATION), flank pain, gynecomastia; Respiratory: Pulmonary infiltrates, eosinophilic pneumonitis, bronchospasm, pneumonia, bronchitis, rhinorrhea, sore throat and hoarseness, asthma, upper respiratory infection; Skin: Exfoliative dermatitis, toxic epidermal necrolysis, Stevens-Johnson syndrome, herpes zoster, erythema multiforme, urticaria, pemphigus, alopecia, flushing, photosensitivity; Special Senses: Blurred vision, taste alteration, anosmia, conjunctivitis, dry eyes, tearing.

Miscellaneous: A symptom complex has been reported which may include some or all of the following: a positive ANA, an elevated erythrocyte sedimentation rate, arthralgia/arthritis, myalgia/myositis, fever, serositis, vasculitis, leukocytosis, eosinophilia, photosensitivity, rash and other dermatologic manifestations.

Hydrochlorothiazide – Body as a Whole: Weakness; Digestive: Pancreatitis, jaundice (intrahepatic cholestatic jaundice), sialadenitis, cramping, gastric irritation, anorexia; Hematologic: Aplastic anemia, agranulocytosis, leukopenia, hemolytic anemia, thrombocytopenia; Hypersensitivity: Purpura, photosensitivity, urticaria, necrotizing angiitis (vasculitis and cutaneous vasculitis), fever, respiratory distress including pneumonitis and pulmonary edema, anaphylactic reactions; Musculoskeletal: Muscle spasm; Nervous System/Psychiatric: Restlessness; Renal: Renal failure, renal dysfunction, interstitial nephritis (see WARNINGS); Skin: Erythema multiforme including Stevens-Johnson syndrome, exfoliative dermatitis including toxic epidermal necrolysis, alopecia; Special Senses: Transient blurred vision, xanthopsia.

Postmarketing Experience

Non-melanoma Skin Cancer: Hydrochlorothiazide is associated with an increased risk of non-melanoma skin cancer. In a study conducted in the Sentinel System, increased risk was predominantly for squamous cell carcinoma (SCC) and in white patients taking large cumulative doses. The increased risk for SCC in the overall population was approximately 1 additional case per 16,000 patients per year, and for white patients taking a cumulative dose of ≥50,000 mg the risk increase was approximately 1 additional SCC case for every 6,700 patients per year.

To report SUSPECTED ADVERSE REACTIONS, contact Bausch Health US, LLC at 1-800-321-4576 or FDA at 1-800-FDA-1088 or www.fda.gov/medwatch.

OVERDOSAGE

No specific information is available on the treatment of overdosage with VASERETIC. Treatment is symptomatic and supportive. Therapy with VASERETIC should be discontinued and the patient observed closely. Suggested measures include induction of emesis and/or gastric lavage, and correction of dehydration, electrolyte imbalance and hypotension by established procedures.

Enalapril Maleate – Single oral doses of enalapril above 1,000 mg/kg and ≥ 1,775 mg/kg were associated with lethality in mice and rats, respectively. The most likely manifestation of overdosage would be hypotension, for which the usual treatment would be intravenous infusion of normal saline solution. Enalaprilat may be removed from general circulation by hemodialysis and has been removed from neonatal circulation by peritoneal dialysis (see WARNINGS, Anaphylactoid Reactions During Membrane Exposure).

Hydrochlorothiazide – Lethality was not observed after administration of an oral dose of 10 g/kg to mice and rats. The most common signs and symptoms observed are those caused by electrolyte depletion (hypokalemia, hypochloremia, hyponatremia) and dehydration resulting from excessive diuresis. If digitalis has also been administered, hypokalemia may accentuate cardiac arrhythmias.

DOSAGE AND ADMINISTRATION

Enalapril and hydrochlorothiazide are effective treatments for hypertension. The usual dosage range of enalapril is 10 to 40 mg per day administered in a single or two divided doses; hydrochlorothiazide is effective in doses of 12.5 to 50 mg daily. The side effects (see WARNINGS) of enalapril are generally rare and apparently independent of dose; those of hydrochlorothiazide are a mixture of dose-dependent phenomena (primarily hypokalemia) and dose-independent phenomena (e.g., pancreatitis), the former much more common than the latter. Therapy with any combination of enalapril and hydrochlorothiazide will be associated with both sets of dose-independent side effects but the addition of enalapril in clinical trials blunted the hypokalemia normally seen with diuretics. To minimize dose-independent side effects, it is usually appropriate to begin combination therapy only after a patient has failed to achieve the desired effect with monotherapy.

Dose Titration Guided by Clinical Effect: A patient whose blood pressure is not adequately controlled with either enalapril or hydrochlorothiazide monotherapy may be given VASERETIC 10-25 mg. Further increases of enalapril, hydrochlorothiazide or both depend on clinical response. The hydrochlorothiazide dose should generally not be increased until 2-3 weeks have elapsed. In general, patients do not require doses in excess of 20 mg of enalapril or 50 mg of hydrochlorothiazide. The daily dosage should not exceed two tablets of VASERETIC 10-25 mg.

Replacement Therapy: The combination may be substituted for the titrated components.

Use in Renal Impairment: The usual regimens of therapy with VASERETIC need not be adjusted as long as the patient's creatinine clearance is greater than 30 mL/min/1.73 m^2 (serum creatinine approximately less than or equal to 3 mg/dL or 265 µmol/L). In patients with more severe renal impairment, loop diuretics are preferred to thiazides, so enalapril maleate and hydrochlorothiazide is not recommended (see WARNINGS, Anaphylactoid Reactions During Membrane Exposure).

HOW SUPPLIED

VASERETIC Tablets 10-25 mg are rust-colored, oval-shaped tablets with one side imprinted with “VASE 10-25” and both sides scored. Each tablet contains 10 mg of enalapril maleate and 25 mg of hydrochlorothiazide. They are supplied as follows:

NDC 0187-0146-01 bottles of 100 (with desiccant).

STORAGE AND HANDLING

Storage: Store at 25°C (77°F); excursions permitted to 15° to 30°C (59° to 86°F) [see USP Controlled Room Temperature].

Keep container tightly closed.

Protect from moisture.

Dispense in a tight container as per USP, if product package is subdivided.

Distributed by:
Bausch Health US, LLC
Bridgewater, NJ 08807 USA

Manufactured by:
Bausch Health Companies Inc.
Steinbach, MB R5G 1Z7, Canada

VASERETIC is a trademark of Bausch Health Companies Inc. or its affiliates.

© 2020 Bausch Health Companies Inc. or its affiliates

Rev. 09/2020

9390805_ 20002950

PRINCIPAL DISPLAY PANEL - 100 Tablet Bottle Label

NDC 0187-0146-01

Rx only

Vaseretic®
(enalapril maleate and hydrochlorothiazide)
Tablets

10/25 mg

100 Tablets

BAUSCH Health